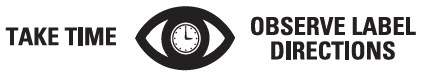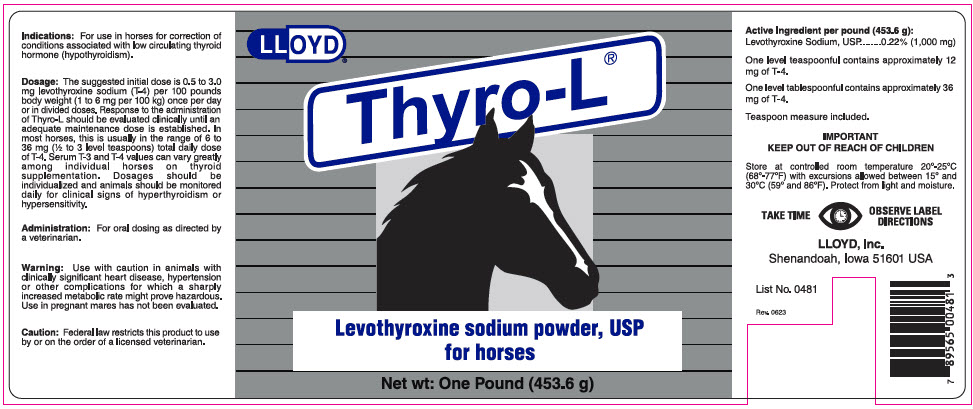 DRUG LABEL: Thyro-L
NDC: 11789-048 | Form: POWDER
Manufacturer: LLOYD, Inc. of Iowa
Category: animal | Type: PRESCRIPTION ANIMAL DRUG LABEL
Date: 20230927

ACTIVE INGREDIENTS: LEVOTHYROXINE SODIUM 1000 mg/453.6 g

Thyro-L®

VETERINARY INDICATIONS

Indications: For use in horses for correction of conditions associated with low circulating thyroid hormone (hypothyroidism).

DOSAGE AND ADMINISTRATION

Dosage: The suggested initial dose is 0.5 to 3.0 mg levothyroxine sodium (T-4) per 100 pounds body weight (1 to 6 mg per 100 kg) once per day or in divided doses. Response to the administration of Thyro-L should be evaluated clinically until an adequate maintenance dose is established. In most horses, this is usually in the range of 6 to 36 mg (½ to 3 level teaspoons) total daily dose of T-4. Serum T-3 and T-4 values can vary greatly among individual horses on thyroid supplementation. Dosages should be individualized and animals should be monitored daily for clinical signs of hyperthyroidism or hypersensitivity.

DOSAGE AND ADMINISTRATION

Administration: For oral dosing as directed by a veterinarian.

WARNINGS

Warning: Use with caution in animals with clinically significant heart disease, hypertension or other complications for which a sharply increased metabolic rate might prove hazardous. Use in pregnant mares has not been evaluated.

SAFE HANDLING WARNING

Caution: Federal law restricts this product to use by or on the order of a licensed veterinarian.

Active Ingredient per pound (453.6 g):

Levothyroxine Sodium, USP | 0.22% (1,000 mg)

One level teaspoonful contains approximately 12 mg of T-4.

One level tablespoonful contains approximately 36 mg of T-4.

Teaspoon measure included.

IMPORTANT
KEEP OUT OF REACH OF CHILDREN

STORAGE AND HANDLING

Store at controlled room temperature 20°-25°C (68°-77°F) with excursions allowed between 15° and 30°C (59° and 86°F). Protect from light and moisture.

LLOYD, Inc.
Shenandoah, Iowa 51601 USA

List No. 0481
Rev. 0623

PRINCIPAL DISPLAY PANEL - 453.6 g Bottle Label

LLOYD®

Thyro-L®

Levothyroxine sodium powder, USP
for horses

Net wt: One Pound (453.6 g)